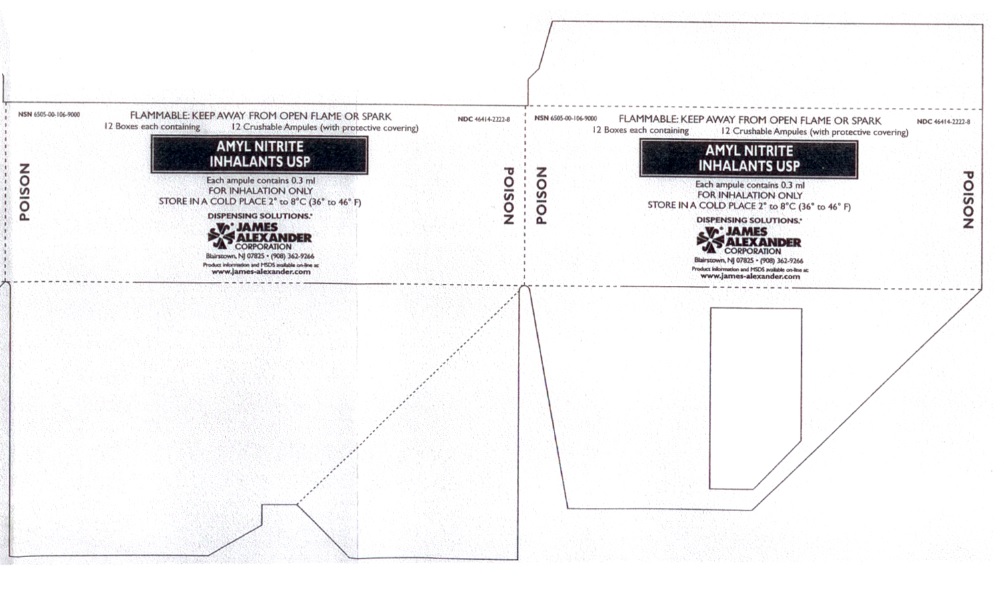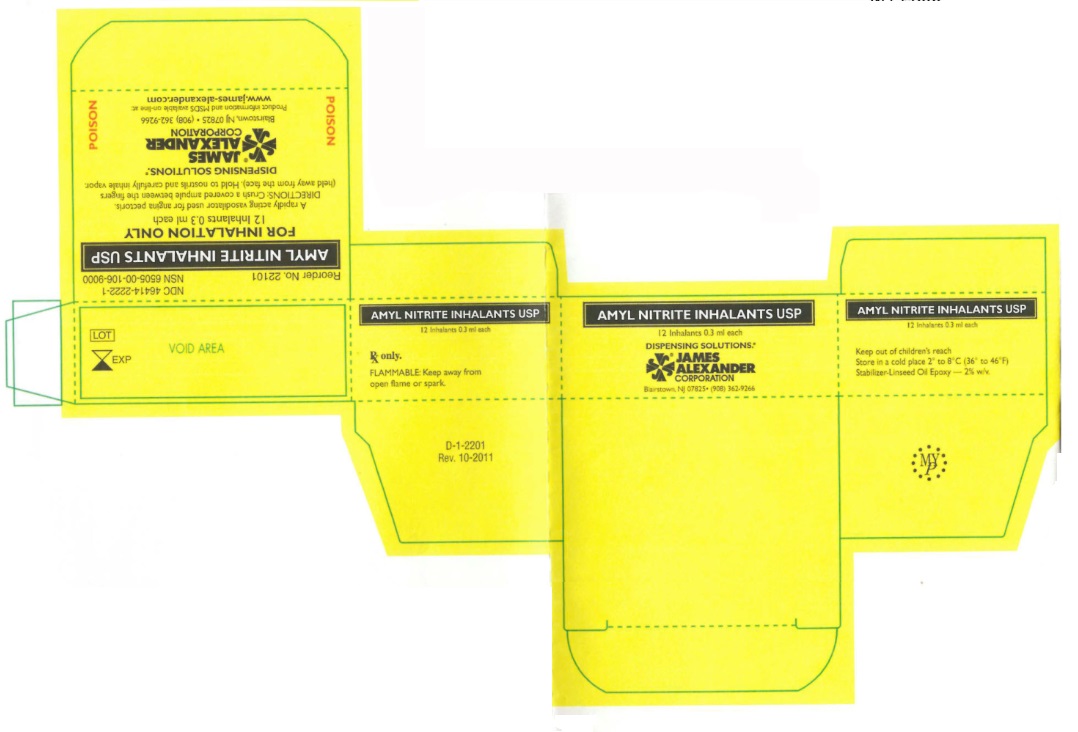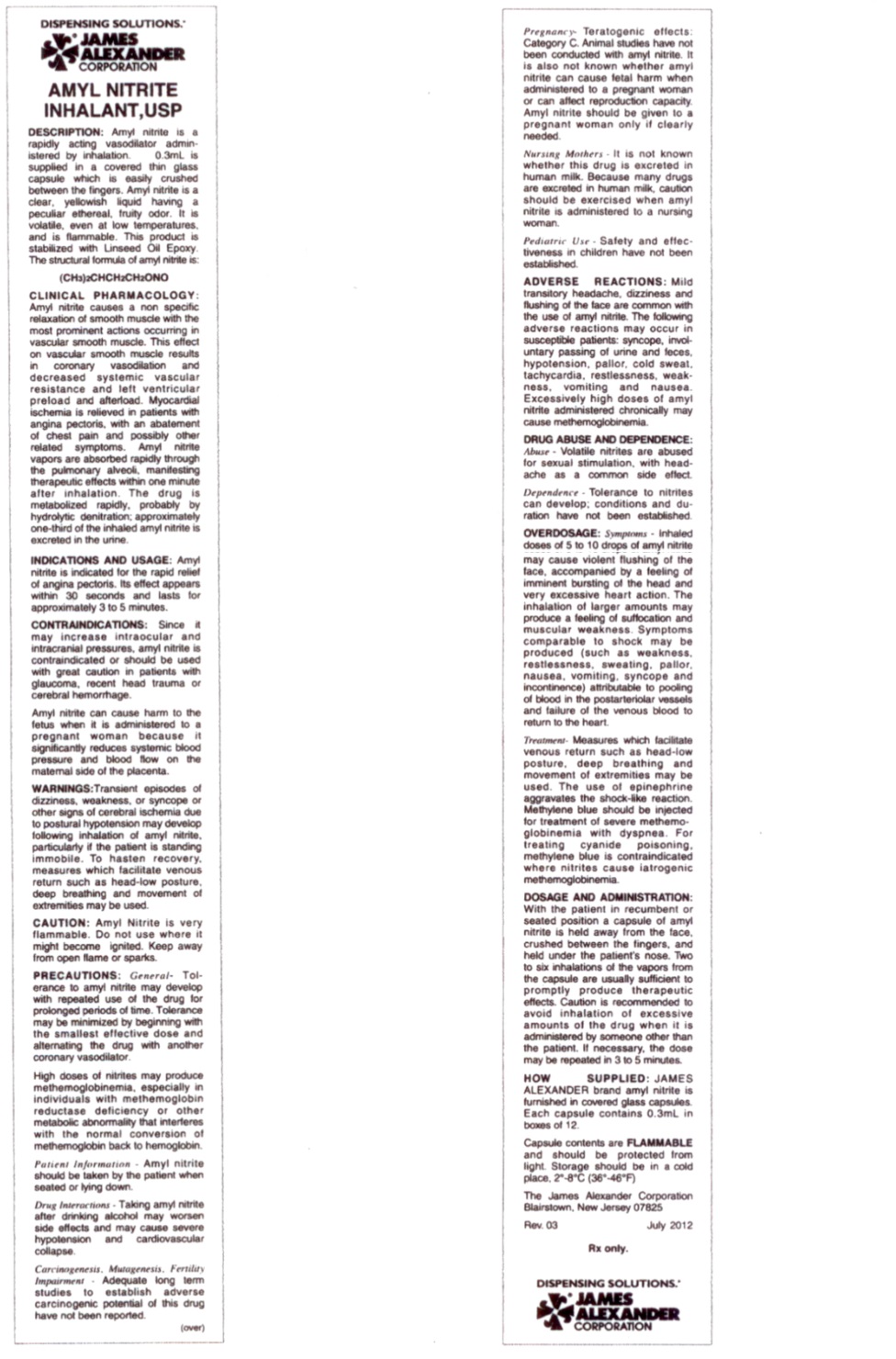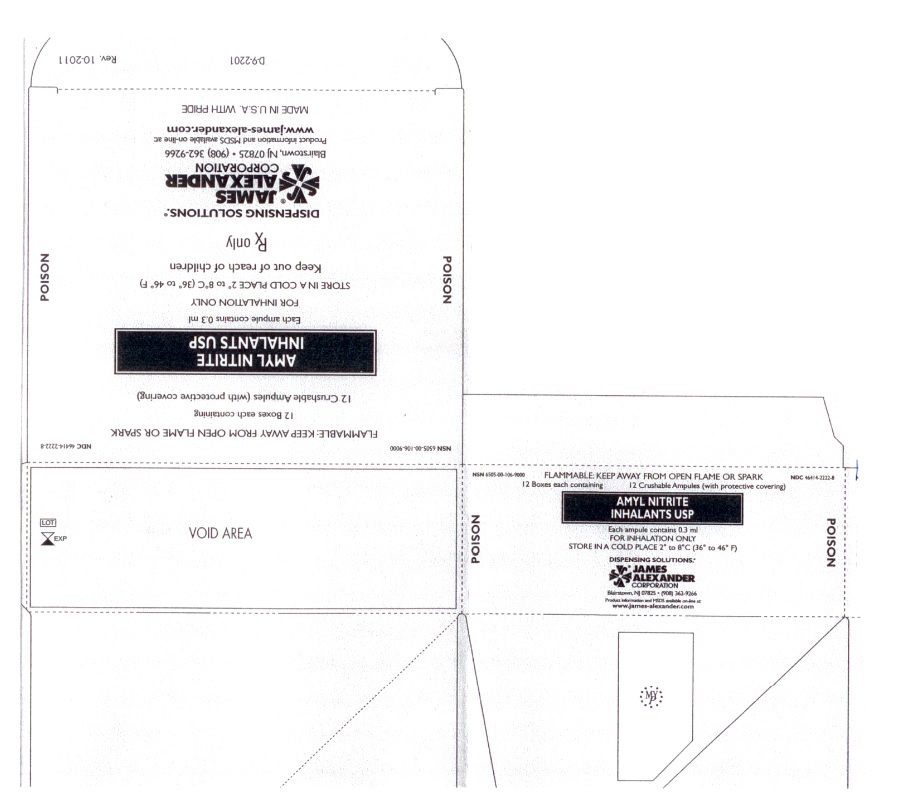 DRUG LABEL: Amyl Nitrite
NDC: 46414-2222 | Form: INHALANT
Manufacturer: James Alexander Corporation
Category: prescription | Type: HUMAN PRESCRIPTION DRUG LABEL
Date: 20190205

ACTIVE INGREDIENTS: AMYL NITRITE 0.3 g/0.3 mL
INACTIVE INGREDIENTS: LINSEED OIL

AMYL NITRITE INHALANTS USP

DESCRIPTION:

Amyl nitrite is a rapidly acting vasodilator administered by inhalation. 0.3mL is supplied in a covered thin glass capsule which is easily crushed between the fingers. Amyl nitrite is a clear, yellowish liquid having a peculiar ethereal, fruity odor. It is volatile, even at low temperatures, and is flammable. This product is stabilized with Linseed Oil Epoxy. The structural formula of amyl nitrite is:

(CH3)2CHCH2CH2ONO

CLINICAL PHARMACOLOGY:

Amyl nitrite causes a non specific relaxation of smooth muscle with the most prominent actions occurring in vascular smooth muscle. This effect on vascular smooth muscle results in coronary vasodilation and decreased systemic vascular resistance and left ventricular preload and afterload. Myocardial ischemia is relieved in patients with angina pectoris, with an abatement of chest pain and possibly other related symptoms. Amyl nitrite vapors are absorbed rapidly through the pulmonary alveoli, manifesting therapeutic effects within one minute after inhalation. The drug is metabolized rapidly, probably by hydrolytic denitration; approximately one-third of the inhaled amyl nitrite is excreted in the urine.

INDICATIONS AND USAGE:

Amyl nitrite is indicated for the rapid relief of angina pectoris. Its effect appears within 30 seconds and lasts for approximately 3 to 5 minutes.

CONTRAINDICATIONS:

Since it may increase intraocular and intracranial pressures, amyl nitrite is contraindicated or should be used with great caution in patients with glaucoma, recent head trauma or cerebral hemorrhage.

Amyl nitrite can cause harm to the fetus when it is administered to a pregnant woman because it significantly reduces systemic blood pressure and blood flow on the maternal side of the placenta.

WARNINGS:

Transient episodes of dizziness, weakness, or syncope or other signs of cerebral ischemia due to postural hypotension may develop following inhalation of amyl nitrite, particularly if the patient is standing immobile. To hasten recovery, measures which facilitate venous return such as head low posture, deep breathing and movement of extremities may be used.

PRECAUTIONS

CAUTION: Amyl nitrite is very flammable. Do not use where it might become ignited. Keep away from open flame or sparks.

PRECAUTIONS: General - Tolerance to amyl nitrite may develop with repeated use of the drug for prolonged periods of time. Tolerance may be minimized by beginning with the smallest effective dose and alternating the drug with another coronary vasodilator.

High doses of nitrites may produce methemoglobinemia, especially in individuals with methemoglobin reductase deficiency or other metabolic abnormality that interferes with the normal conversion of methemoglobin back to haemoglobin.

Patient Information - Amyl nitrite should be taken by the patient when seated or lying down.

Drug Interactions - Taking amyl nitrite after drinking alcohol may worsen side effects and may cause severe hypotension and cardiovascular collapse.

Carcinogenesis, Mutagenesis, Fertility Impairment - Adequate long term studies to establish adverse carcinogenic potential of this drug have not been reported.

Pregnancy - Teratogenic effects: Category C. Animal studies have not been conducted with amyl nitrite. It is also not known whether amyl nitrite can cause fetal harm when administered to a pregnant woman or can affect reproduction capacity. Amyl nitrite should be given to a pregnant woman only if clearly needed.

Nursing Mothers - It is not known whether this drug is excreted in human milk. Because many drugs are excreted in human milk, caution should be exercised when amyl nitrite is administered to a nursing woman.

Pediatric Use - Safety and effectiveness in children have not been established.

ADVERSE REACTIONS:

Mild transitory headache, dizziness and flushing of the face are common with the use of amyl nitrite. The following adverse reactions may occur in susceptible patients: syncope, involuntary passing of urine and feces, hypotension, pallor, cold sweat, tachycardia, restlessness, weakness, vomiting and nausea. Excessively high doses of amyl nitrite administered chronically may cause methemoglobinemia.

DRUG ABUSE AND DEPENDENCE:

Abuse - Volatile nitrites are abused for sexual stimulation, with headache as a common side effect.

Dependence - Tolerance to nitrites can develop; conditions and duration have not been established.

OVERDOSAGE:

Symptoms - Inhaled doses of 5 to 10 drops of amyl nitrite may cause violent flushing of the face, accompanied by a feeling of imminent bursting of the head and very excessive heart action. The inhalation of larger amounts may produce a feeling of suffocation and muscular weakness. Symptoms comparable to shock may be produced (such as weakness, restlessness, sweating, pallor, nausea, vomiting, syncope and incontinence) attributable to pooling of blood in the postarteriolar vessels and failure of the venous blood to return to the heart.

Treatment - Measures which facilitate venous return such as head-low posture, deep breathing and movement of extremities may be used. The use of epinephrine aggravates the shock- like reaction. Methylene blue should be injected for treatment of severe methemoglobinemia with dyspnea. For treating cyanide poisoning, methylene blue is contraindicated where nitrites cause iatrogenic methemoglobinemia.

DOSAGE & ADMINISTRATION:

With the patient in recumbent or seated position a capsule of amyl nitrite is held away from the face, crushed between the fingers, and held under the patient's nose. Two to six inhalations of the vapors from the capsule are usually sufficient to promptly produce therapeutic effects. Caution is recommended to avoid inhalation of excessive amounts of the drug when it is administered by someone other than the patient. If necessary, the dose may be repeated in 3 to 5 minutes.

HOW SUPPLIED:

JAMES ALEXANDER brand amyl nitrite is furnished in covered glass capsules. Each capsule contains 0.3 mL in boxes of 12.

Capsule contents are FLAMMABLE and should be protected from light. Storage should be in a cold place. 2o - 8oC (36o- 46oF)

The James Alexander Corporation Blairstown, New Jersey 07825.

Rev. 03 July 2012

Rx only.

DISPENSING SOLUTIONS®

JAMES ALEXANDER CORPORATION
Blairstown, NJ. (908) 362-9266
Product information and MSDS available on-line at
www.james-alexander.com